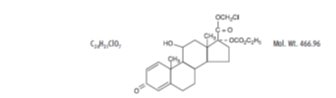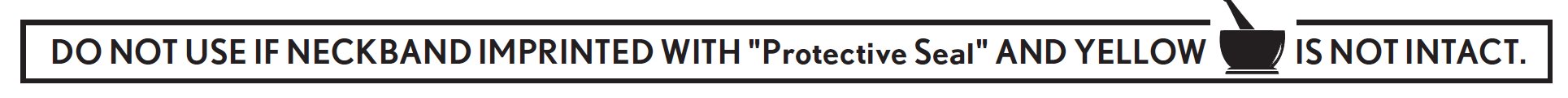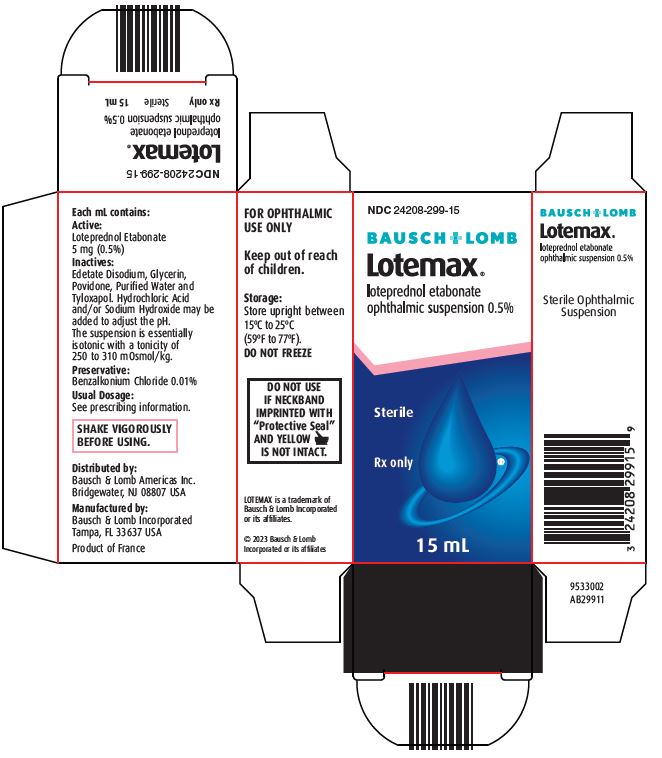 DRUG LABEL: LOTEMAX
NDC: 24208-299 | Form: SUSPENSION/ DROPS
Manufacturer: Bausch & Lomb Incorporated
Category: prescription | Type: HUMAN PRESCRIPTION DRUG LABEL
Date: 20230417

ACTIVE INGREDIENTS: LOTEPREDNOL ETABONATE 5 mg/1 mL
INACTIVE INGREDIENTS: BENZALKONIUM CHLORIDE 0.1 mg/1 mL; EDETATE DISODIUM; GLYCERIN; WATER; TYLOXAPOL; HYDROCHLORIC ACID; SODIUM HYDROXIDE; POVIDONE, UNSPECIFIED

Lotemax®
loteprednol etabonate
ophthalmic suspension 0.5%
STERILE OPHTHALMIC SUSPENSION
Rx only

DESCRIPTION

LOTEMAX® (loteprednol etabonate ophthalmic suspension) contains a sterile, topical anti-inflammatory corticosteroid for ophthalmic use. Loteprednol etabonate is a white to off-white powder.

Loteprednol etabonate is represented by the following structural formula:

Chemical Name:

chloromethyl 17α-[(ethoxycarbonyl)oxy]-11β-hydroxy-3-oxoandrosta-1,4-diene-17β-carboxylate

Each mL contains:

Active: Loteprednol Etabonate 5 mg (0.5%)

Inactives: Edetate Disodium, Glycerin, Povidone, Purified Water and Tyloxapol. Hydrochloric Acid and/or Sodium Hydroxide may be added to adjust the pH. The suspension is essentially isotonic with a tonicity of 250 to 310 mOsmol/kg.

Preservative: Benzalkonium Chloride 0.01%

CLINICAL PHARMACOLOGY

Corticosteroids inhibit the inflammatory response to a variety of inciting agents and probably delay or slow healing. They inhibit the edema, fibrin deposition, capillary dilation, leukocyte migration, capillary proliferation, fibroblast proliferation, deposition of collagen, and scar formation associated with inflammation. There is no generally accepted explanation for the mechanism of action of ocular corticosteroids. However, corticosteroids are thought to act by the induction of phospholipase A2 inhibitory proteins, collectively called lipocortins. It is postulated that these proteins control the biosynthesis of potent mediators of inflammation such as prostaglandins and leukotrienes by inhibiting the release of their common precursor arachidonic acid. Arachidonic acid is released from membrane phospholipids by phospholipase A2. Corticosteroids are capable of producing a rise in intraocular pressure (IOP).

Loteprednol etabonate is structurally similar to other corticosteroids. However, the number 20 position ketone group is absent. It is highly lipid soluble which enhances its penetration into cells. Loteprednol etabonate is synthesized through structural modifications of prednisolone-related compounds so that it will undergo a predictable transformation to an inactive metabolite. Based upon in vivoand in vitropreclinical metabolism studies, loteprednol etabonate undergoes extensive metabolism to inactive carboxylic acid metabolites.

Results from a bioavailability study in normal volunteers established that plasma levels of loteprednol etabonate and Δ^1 cortienic acid etabonate (PJ 91), its primary, inactive metabolite, were below the limit of quantitation (1 ng/mL) at all sampling times. The results were obtained following the ocular administration of one drop in each eye of 0.5% loteprednol etabonate 8 times daily for 2 days or 4 times daily for 42 days. This study suggests that limited (<1 ng/mL) systemic absorption occurs with LOTEMAX.

Clinical Studies

Post-Operative Inflammation:Placebo-controlled clinical studies demonstrated that LOTEMAX is effective for the treatment of anterior chamber inflammation as measured by cell and flare.

Giant Papillary Conjunctivitis:Placebo-controlled clinical studies demonstrated that LOTEMAX was effective in reducing the signs and symptoms of giant papillary conjunctivitis after 1 week of treatment and continuing for up to 6 weeks while on treatment.

Seasonal Allergic Conjunctivitis:A placebo-controlled clinical study demonstrated that LOTEMAX was effective in reducing the signs and symptoms of allergic conjunctivitis during peak periods of pollen exposure.

Uveitis:Controlled clinical studies of patients with uveitis demonstrated that LOTEMAX was less effective than prednisolone acetate 1%. Overall, 72% of patients treated with LOTEMAX experienced resolution of anterior chamber cell by day 28, compared to 87% of patients treated with 1% prednisolone acetate. The incidence of patients with clinically significant increases in IOP (≥10 mmHg) was 1% with LOTEMAX and 6% with prednisolone acetate 1%.

INDICATIONS AND USAGE

LOTEMAX is indicated for the treatment of steroid-responsive inflammatory conditions of the palpebral and bulbar conjunctiva, cornea and anterior segment of the globe such as allergic conjunctivitis, acne rosacea, superficial punctate keratitis, herpes zoster keratitis, iritis, cyclitis, selected infective conjunctivitides, when the inherent hazard of steroid use is accepted to obtain an advisable diminution in edema and inflammation.

LOTEMAX is less effective than prednisolone acetate 1% in two 28-day controlled clinical studies in acute anterior uveitis, where 72% of patients treated with LOTEMAX experienced resolution of anterior chamber cells, compared to 87% of patients treated with prednisolone acetate 1%. The incidence of patients with clinically significant increases in IOP (≥10 mmHg) was 1% with LOTEMAX and 6% with prednisolone acetate 1%. LOTEMAX should not be used in patients who require a more potent corticosteroid for this indication.

LOTEMAX is also indicated for the treatment of post-operative inflammation following ocular surgery.

CONTRAINDICATIONS

LOTEMAX, as with other ophthalmic corticosteroids, is contraindicated in most viral diseases of the cornea and conjunctiva including epithelial herpes simplex keratitis (dendritic keratitis), vaccinia, and varicella, and also in mycobacterial infection of the eye and fungal diseases of ocular structures. LOTEMAX is also contraindicated in individuals with known or suspected hypersensitivity to any of the ingredients of this preparation and to other corticosteroids.

WARNINGS

Prolonged use of corticosteroids may result in glaucoma with damage to the optic nerve, defects in visual acuity and fields of vision, and in posterior subcapsular cataract formation. Steroids should be used with caution in the presence of glaucoma.

Prolonged use of corticosteroids may suppress the host response and thus increase the hazard of secondary ocular infections. In those diseases causing thinning of the cornea or sclera, perforations have been known to occur with the use of topical steroids. In acute purulent conditions of the eye, steroids may mask infection or enhance existing infection.

Use of ocular steroids may prolong the course and may exacerbate the severity of many viral infections of the eye (including herpes simplex). Employment of a corticosteroid medication in the treatment of patients with a history of herpes simplex requires great caution.

The use of steroids after cataract surgery may delay healing and increase the incidence of bleb formation.

PRECAUTIONS

General

For ophthalmic use only. The initial prescription and renewal of the medication order beyond 14 days should be made by a physician only after examination of the patient with the aid of magnification, such as slit lamp biomicroscopy and, where appropriate, fluorescein staining.

If signs and symptoms fail to improve after two days, the patient should be re-evaluated.

If this product is used for 10 days or longer, intraocular pressure should be monitored even though it may be difficult in children and uncooperative patients (see WARNINGS).

Fungal infections of the cornea are particularly prone to develop coincidentally with long-term local steroid application. Fungus invasion must be considered in any persistent corneal ulceration where a steroid has been used or is in use. Fungal cultures should be taken when appropriate.

Information for Patients

This product is sterile when packaged. Patients should be advised not to allow the dropper tip to touch any surface, as this may contaminate the suspension. If pain develops, redness, itching or inflammation becomes aggravated, the patient should be advised to consult a physician. As with all ophthalmic preparations containing benzalkonium chloride, patients should be advised not to wear soft contact lenses when using LOTEMAX suspension.

Carcinogenesis, Mutagenesis, Impairment of Fertility

Long-term animal studies have not been conducted to evaluate the carcinogenic potential of loteprednol etabonate. Loteprednol etabonate was not genotoxic in vitroin the Ames test, the mouse lymphoma tk assay, or in a chromosome aberration test in human lymphocytes, or in vivoin the single dose mouse micronucleus assay. Treatment of male and female rats with up to 50 mg/kg/day and 25 mg/kg/day of loteprednol etabonate, respectively, (600 and 300 times the maximum clinical dose, respectively) prior to and during mating did not impair fertility in either gender.

Pregnancy

Teratogenic effects

Loteprednol etabonate has been shown to be embryotoxic (delayed ossification) and teratogenic (increased incidence of meningocele, abnormal left common carotid artery, and limb flexures) when administered orally to rabbits during organogenesis at a dose of 3 mg/kg/day (35 times the maximum daily clinical dose), a dose which caused no maternal toxicity. The no-observed-effect-level (NOEL) for these effects was 0.5 mg/kg/day (6 times the maximum daily clinical dose). Oral treatment of rats during organogenesis resulted in teratogenicity (absent innominate artery at ≥5 mg/kg/day doses, and cleft palate and umbilical hernia at ≥50 mg/kg/day) and embryotoxicity (increased post-implantation losses at 100 mg/kg/day and decreased fetal body weight and skeletal ossification with ≥50 mg/kg/day). Treatment of rats with 0.5 mg/kg/day (6 times the maximum clinical dose) during organogenesis did not result in any reproductive toxicity. Loteprednol etabonate was maternally toxic (significantly reduced body weight gain during treatment) when administered to pregnant rats during organogenesis at doses of ≥5 mg/kg/day.

Oral exposure of female rats to 50 mg/kg/day of loteprednol etabonate from the start of the fetal period through the end of lactation, a maternally toxic treatment regimen (significantly decreased body weight gain), gave rise to decreased growth and survival, and retarded development in the offspring during lactation; the NOEL for these effects was 5 mg/kg/day. Loteprednol etabonate had no effect on the duration of gestation or parturition when administered orally to pregnant rats at doses up to 50 mg/kg/day during the fetal period.

Nursing Mothers

It is not known whether topical ophthalmic administration of corticosteroids could result in sufficient systemic absorption to produce detectable quantities in human milk. Systemic steroids appear in human milk and could suppress growth, interfere with endogenous corticosteroid production, or cause other untoward effects. Caution should be exercised when LOTEMAX is administered to a nursing woman.

Pediatric Use

Safety and effectiveness in pediatric patients have not been established.

ADVERSE REACTIONS

Reactions associated with ophthalmic steroids include elevated intraocular pressure, which may be associated with optic nerve damage, visual acuity and field defects, posterior subcapsular cataract formation, secondary ocular infection from pathogens including herpes simplex, and perforation of the globe where there is thinning of the cornea or sclera.

Ocular adverse reactions occurring in 5%-15% of patients treated with loteprednol etabonate ophthalmic suspension (0.2%-0.5%) in clinical studies included abnormal vision/blurring, burning on instillation, chemosis, discharge, dry eyes, epiphora, foreign body sensation, itching, injection, and photophobia. Other ocular adverse reactions occurring in less than 5% of patients include conjunctivitis, corneal abnormalities, eyelid erythema, keratoconjunctivitis, ocular irritation/pain/discomfort, papillae, and uveitis. Some of these events were similar to the underlying ocular disease being studied.

Non-ocular adverse reactions occurred in less than 15% of patients. These include headache, rhinitis and pharyngitis.

In a summation of controlled, randomized studies of individuals treated for 28 days or longer with loteprednol etabonate, the incidence of significant elevation of intraocular pressure (≥10 mmHg) was 2% (15/901) among patients receiving loteprednol etabonate, 7% (11/164) among patients receiving 1% prednisolone acetate and 0.5% (3/583) among patients receiving placebo.

To report SUSPECTED ADVERSE REACTIONS, contact Bausch & Lomb Incorporated at 1-800-553-5340 or FDA at 1-800-FDA-1088 or www.fda.gov/medwatch.

DOSAGE AND ADMINISTRATION

SHAKE VIGOROUSLY BEFORE USING.

Steroid-Responsive Disease Treatment: Apply one to two drops of LOTEMAX suspension into the conjunctival sac of the affected eye four times daily. During the initial treatment within the first week, the dosing may be increased, up to 1 drop every hour, if necessary. Care should be taken not to discontinue therapy prematurely. If signs and symptoms fail to improve after two days, the patient should be re-evaluated (see PRECAUTIONS).

Post-Operative Inflammation: Apply one to two drops of LOTEMAX suspension into the conjunctival sac of the operated eye four times daily beginning 24 hours after surgery and continuing throughout the first 2 weeks of the post-operative period.

HOW SUPPLIED

LOTEMAX® (loteprednol etabonate ophthalmic suspension) is supplied in a plastic bottle with a controlled drop tip in the following sizes:

NDC 24208-299-05 5 mL
NDC 24208-299-10 10 mL
NDC 24208-299-15 15 mL

Storage: Store upright between 15°C to 25°C (59°F to 77°F). DO NOT FREEZE

Keep out of reach of children.

Distributed by:
Bausch & Lomb Americas Inc.
Bridgewater, NJ 08807 USA

Manufactured by:
Bausch & Lomb Incorporated
Tampa, FL 33637 USA

LOTEMAX is a trademark of Bausch & Lomb Incorporated or its affiliates.

© 2023 Bausch & Lomb Incorporated or its affiliates

Revised: April 2023

9007808 (Folded)

9005908 (Flat)

PACKAGE/LABEL PRINCIPAL DISPLAY PANEL

NDC 24208-299-15

BAUSCH + LOMB

Lotemax®

loteprednol etabonate
ophthalmic suspension 0.5%

Sterile

Rx only

15 mL